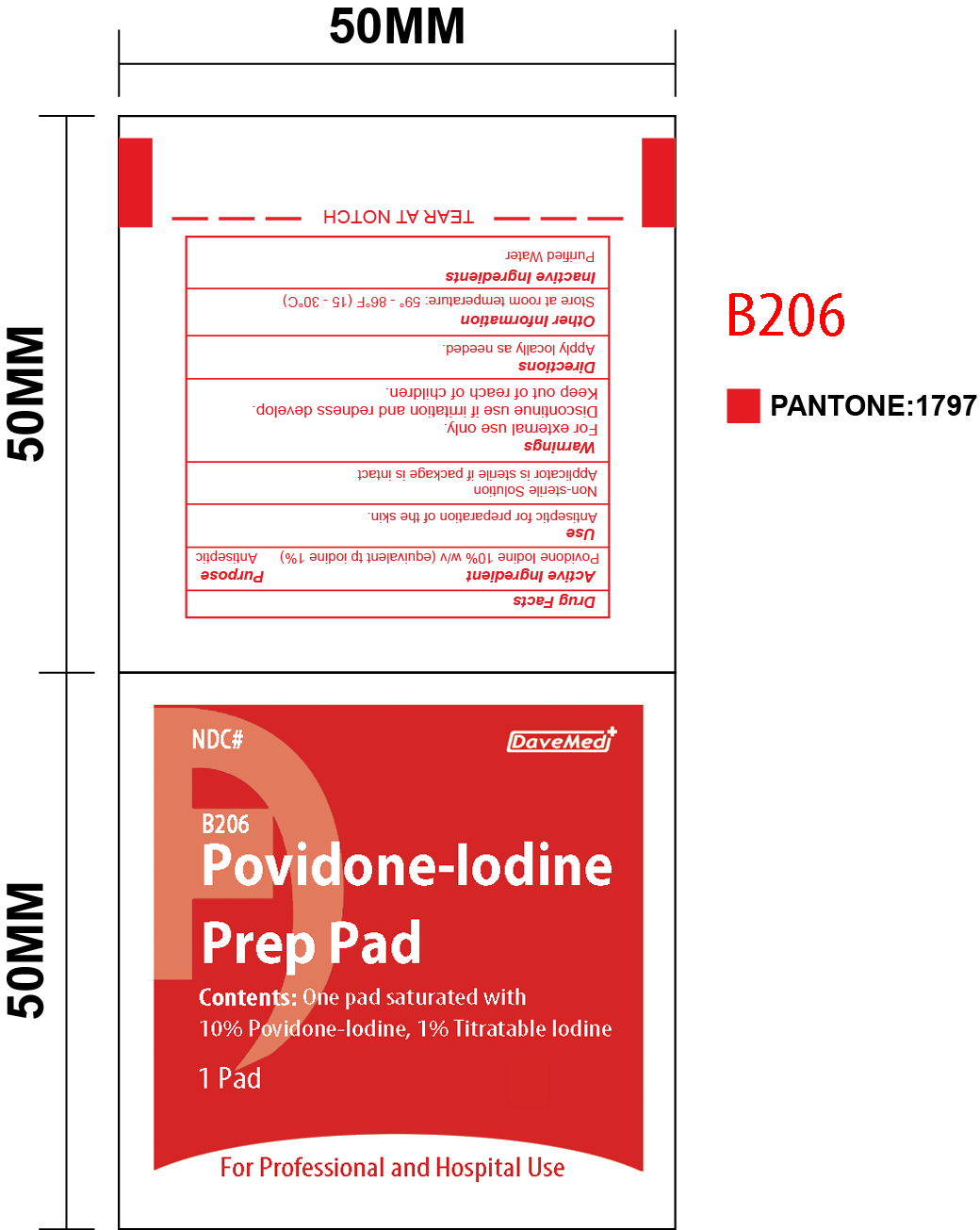 DRUG LABEL: Povidone-Iodine Prep Pad
NDC: 70897-006 | Form: SWAB
Manufacturer: Davemed Healthcare Co., Ltd
Category: otc | Type: HUMAN OTC DRUG LABEL
Date: 20190124

ACTIVE INGREDIENTS: POVIDONE-IODINE 0.1 mg/1 1
INACTIVE INGREDIENTS: WATER

Povidone-Iodine

Active Ingredient

Povidone Iodine 10% w/w (equivalent to iodine 1%)

Purpose

Antiseptic

Use

Antiseptic for preparation of the skin.

Non-sterile Solution

Applicator is sterile if package is intact

Warnings

For external use only.
Discontinue use if irritation and redness develop.

Keep out of reach of Children.

Directions

Apply locally as needed.

Inactive ingredients

Purified Water